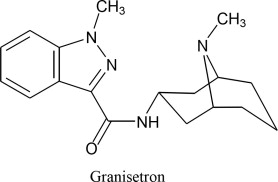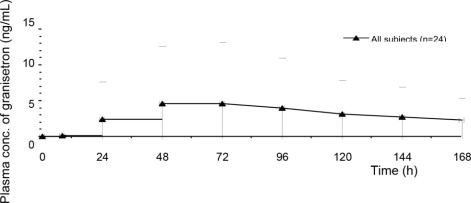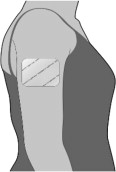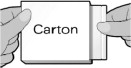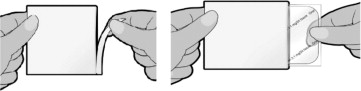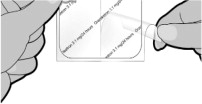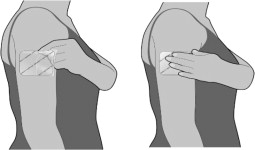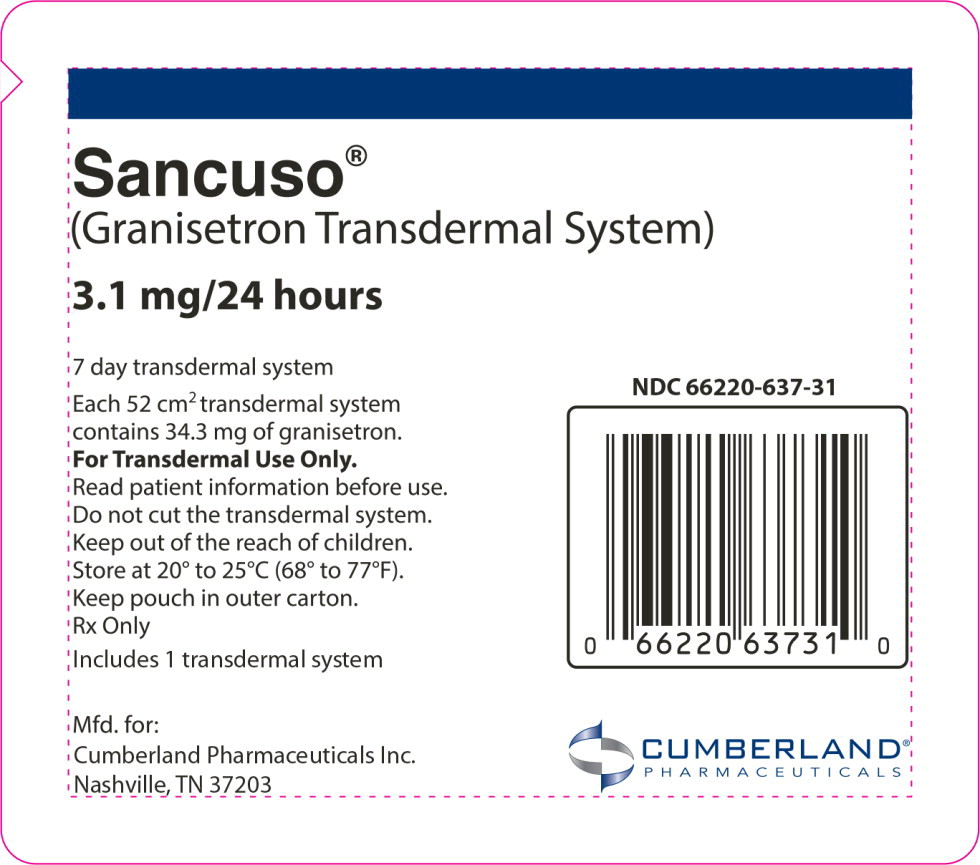 DRUG LABEL: SANCUSO
NDC: 66220-637 | Form: PATCH
Manufacturer: Cumberland Pharmaceuticals Inc.
Category: prescription | Type: HUMAN PRESCRIPTION DRUG LABEL
Date: 20241104

ACTIVE INGREDIENTS: granisetron 3.1 mg/24 h

HIGHLIGHTS OF PRESCRIBING INFORMATION

These highlights do not include all the information needed to use SANCUSO safely and effectively. See full prescribing information for SANCUSO.
SANCUSO (granisetron transdermal system)
Initial U.S. Approval: 2008

1 INDICATIONS AND USAGE

SANCUSO is a serotonin-3 (5-HT3) receptor antagonist indicated for the prevention of nausea and vomiting in adults receiving moderately and/or highly emetogenic chemotherapy for up to 5 consecutive days. (1)

2 DOSAGE AND ADMINISTRATION

The recommended dosage is a single transdermal system applied to the upper outer arm a minimum of 24 hours, up to a maximum of 48 hours, before chemotherapy. The transdermal system should be worn at minimum, 24 hours after chemotherapy is finished. The transdermal system can be worn for up to 7 days. (2)

3 DOSAGE FORMS AND STRENGTHS

Transdermal System: 3.1 mg per 24 hours. (3)

4 CONTRAINDICATIONS

Known hypersensitivity to granisetron or to any of the components of the transdermal system (4)

5 WARNINGS AND PRECAUTIONS

- Progressive Ileus and Gastric Distention: Granisetron may mask a progressive ileus and/or gastric distention; consider before use in patients with abdominal surgery.
  Monitor for decreased bowel activity, particularly in patients with risk factors for gastrointestinal obstruction. (5.1)
- Serotonin Syndrome: Serotonin syndrome has been reported with 5-HT3 receptor antagonists alone but particularly with concomitant use of serotonergic drugs. If such symptoms occur, discontinue SANCUSO and initiate supportive treatment. If concomitant use of SANCUSO with other serotonergic drugs is clinically warranted, patients should be aware of a potential increased risk of serotonin syndrome. (5.2, 7.1)
- Skin Reactions: Mild application site reactions have occurred; remove SANCUSO transdermal system if severe reactions or a generalized skin reaction occur. (5.3)
- Increased Drug Exposure with Use of External Heat Sources: Avoid exposing SANCUSO transdermal system and surrounding area to direct external heat sources, such as heating pads (5.4).
- Phototoxicity with Ultraviolet Light Exposure: Avoid direct exposure of application site to natural or artificial sunlight, including sunlamps, by covering with clothing throughout the period of wear and for 10 days after removal. (5.5)

6 ADVERSE REACTIONS

The most common adverse reaction (≥ 3%) is constipation. (6.1)

To report SUSPECTED ADVERSE REACTIONS, contact Cumberland Pharmaceuticals Inc. at 1-877-484-2700 (X 225) or FDA at 1-800-FDA-1088 or www.fda.gov/medwatch.

FULL PRESCRIBING INFORMATION

1 INDICATIONS AND USAGE

SANCUSO® is indicated for the prevention of nausea and vomiting in adults receiving moderately and/or highly emetogenic chemotherapy regimens of up to 5 consecutive days duration.

2 DOSAGE AND ADMINISTRATION

The recommended dosage is a single transdermal system applied to the upper outer arm a minimum of 24 hours, up to a maximum of 48 hours, before chemotherapy. The transdermal system should be worn at minimum, 24 hours after chemotherapy is finished. The transdermal system can be worn for up to 7 days.

Application and Removal Instructions

- Each transdermal system releases 3.1 mg of granisetron per 24 hours for up to 7 days.
- Each transdermal system is packed in a pouch and should be applied directly after the pouch has been opened.
- Only wear one transdermal system at any time.
- Do not cut the transdermal system.
- Open the pouch and apply the transdermal system to clean, dry, nearly hairless, intact healthy skin on the upper outer arm.
- Do not place SANCUSO transdermal system on skin that is red, irritated, or damaged.
- Do not apply a heat pad or heat lamp over or in vicinity of the transdermal system and avoid extended exposure to heat [see Warnings and Precautions (5.4)].
- Cover the application site of the transdermal system with clothing, if there is a risk of exposure to direct natural or artificial sunlight throughout the period of wear and for 10 days following its removal [see Warnings and Precautions (5.5)].
- After the transdermal system is applied, wash hands thoroughly.
- Remove the transdermal system by peeling off gently from the skin.
- Upon removal, fold the transdermal system in half with the sticky side together, and discard in the household trash in a manner that prevents accidental contact or ingestion by children, pets or others.
- SANCUSO contains granisetron. Do not use other granisetron-containing products with SANCUSO.

3 DOSAGE FORMS AND STRENGTHS

Transdermal System: a 52 cm^2 thin, translucent, rectangular-shaped transdermal system with rounded corners imprinted on one side with "Granisetron 3.1 mg/24 hours". The transdermal system releases 3.1 mg of granisetron per 24 hours for up to 7 days.

4 CONTRAINDICATIONS

SANCUSO is contraindicated in patients with known hypersensitivity to granisetron or to any of the components of the transdermal system [see Description (11)].

5 WARNINGS AND PRECAUTIONS

5.1 Progressive Ileus and Gastric Distention

SANCUSO may mask a progressive ileus and/or gastric distention. This should be particularly considered before use of SANCUSO in patients who have had recent abdominal surgery. Monitor for decreased bowel activity, particularly in patients with risk factors for gastrointestinal obstruction.

5.2 Serotonin Syndrome

The development of serotonin syndrome has been reported with 5-HT3 receptor antagonists. Most reports have been associated with concomitant use of serotonergic drugs (e.g., selective serotonin reuptake inhibitors (SSRIs), serotonin and norepinephrine reuptake inhibitors (SNRIs), monoamine oxidase inhibitors, mirtazapine, fentanyl, lithium, tramadol, and intravenous methylene blue). Some of the reported cases were fatal. Serotonin syndrome occurring with overdose of another 5-HT3 receptor antagonist alone has also been reported. The majority of reports of serotonin syndrome related to 5-HT3 receptor antagonist use occurred in a post-anesthesia care unit or an infusion center.

Symptoms associated with serotonin syndrome may include the following combination of signs and symptoms: mental status changes (e.g., agitation, hallucinations, delirium, and coma), autonomic instability (e.g., tachycardia, labile blood pressure, dizziness, diaphoresis, flushing, hyperthermia), neuromuscular symptoms (e.g., tremor, rigidity, myoclonus, hyperreflexia, incoordination), seizures, with or without gastrointestinal symptoms (e.g., nausea, vomiting, diarrhea). Patients should be monitored for the emergence of serotonin syndrome, especially with concomitant use of SANCUSO and other serotonergic drugs. If symptoms of serotonin syndrome occur, discontinue SANCUSO and initiate supportive treatment. Patients should be informed of the increased risk of serotonin syndrome, especially if SANCUSO is used concomitantly with other serotonergic drugs. [see Drug Interactions (7)].

5.3 Skin Reactions

In clinical trials with SANCUSO, application site reactions were reported that were generally mild in intensity and did not lead to discontinuation of use. The incidence of reactions was comparable with placebo.

If severe reactions, or a generalized skin reaction occur (e.g., allergic rash, including erythematous, macular, papular rash or pruritus), remove the SANCUSO transdermal system.

5.4 Increased Drug Exposure with Use of External Heat Sources

Prolonged exposure to heat results in increasing plasma concentrations of granisetron during the period of heat exposure [see Clinical Pharmacology (12.3)]. Do not apply a heat pad or heat lamp over or in the vicinity of the SANCUSO transdermal system and avoid extended exposure to heat [see Dosage and Administration (2)].

5.5 Phototoxicity with Ultraviolet Light Exposure

Granisetron may be affected by direct natural or artificial sunlight, including sunlamps. An in vitro study using Chinese hamster ovary cells suggests that granisetron has the potential for photogenotoxicity [see Nonclinical Toxicology (13.3)]. To avoid a potential skin reaction, advise patients to cover the application site of the transdermal system with clothing if there is a risk of exposure to direct natural or artificial sunlight throughout the period of wear and for 10 days following its removal.

6 ADVERSE REACTIONS

The following are serious or otherwise clinically significant adverse reactions reported in other sections of labeling:

- Progressive ileus and gastric distention [see Warnings and Precautions (5.1)]
- Serotonin syndrome [see Warnings and Precautions (5.2)]
- Skin reactions [see Warnings and Precautions (5.3)]
- Increased drug exposure with use of external heat sources [see Warnings and Precautions (5.4)]
- Phototoxicity with ultraviolet light exposure [se Warnings and Precautions (5.5)]

6.1 Clinical Trials Experience

Because clinical trials are conducted under widely varying conditions, adverse reaction rates observed in the clinical trials of a drug cannot be directly compared to rates in the clinical trials of another drug and may not reflect the rates observed in clinical practice.

The safety of SANCUSO was evaluated in a total of 404 patients undergoing chemotherapy who participated in two double-blind, comparator studies with transdermal system treatment durations of up to 7 days. The control groups included a total of 406 patients who received a daily dose of 2 mg oral granisetron, for 1 to 5 days.

Adverse reactions occurred in 9% (35/404) of patients receiving SANCUSO and 7% (29/406) of patients receiving oral granisetron. The most common adverse reaction was constipation that occurred in 5% of patients in the SANCUSO group and 3% of patients in the oral granisetron group.

Table 1 lists the adverse reactions that occurred in at least 3% of patients treated with SANCUSO or oral granisetron.

Table 1: Incidence of Adverse Reactions in Double-Blind, Active Comparator Controlled Studies in Cancer Patients Receiving Chemotherapy (³ 3% in either group)
 | SANCUSO
 | Transdermal System | Oral granisetron
Body System | N=404 | N=406
Preferred Term | (%) | (%)
Gastrointestinal disorders
Constipation | 5 | 3
Nervous system disorders
Headache | 1 | 3

5-HT3 receptor antagonists, such as granisetron, may be associated with arrhythmias or ECG abnormalities. Three ECGs were performed on 588 patients in a randomized, parallel group, double-blind, double-dummy study: at baseline before treatment, the first day of chemotherapy, and 5 to 7 days after starting chemotherapy. QTcF prolongation greater than 450 milliseconds was seen in a total of 11 (1.9%) patients after receiving granisetron, 8 (2.7%) on oral granisetron, and 3 (1.1%) on the transdermal system. No new QTcF prolongation greater than 480 milliseconds was observed in any patient in this study. No arrhythmias were detected in this study.

Adverse reactions reported in clinical trials with other formulations of granisetron include the following:

Gastrointestinal: abdominal pain, diarrhea, constipation, elevation of ALT and AST levels, nausea and vomiting

Cardiovascular: hypertension, hypotension, angina pectoris, atrial fibrillation and syncope have been observed rarely

Central Nervous System: dizziness, insomnia, headache, anxiety, somnolence and asthenia

Hypersensitivity: rare cases of hypersensitivity reactions, sometimes severe (e.g. anaphylaxis, shortness of breath, hypotension, urticaria) have been reported

Other: fever; events often associated with chemotherapy have also been reported: leucopenia, decreased appetite, anemia, alopecia, thrombocytopenia.

6.2 Postmarketing Experience

The following adverse reactions have been identified during post approval use of SANCUSO. Because these reactions are reported voluntarily from a population of uncertain size, it is not always possible to reliably estimate their frequency or establish a causal relationship to drug exposure.

General Disorders and Administration Site Conditions: Application site reactions (pain, pruritus, erythema, rash, irritation, vesicles, burn, discoloration, urticaria) [see Warnings and Precautions (5.3)]; transdermal system non-adhesion.

Cardiac Disorders: bradycardia, chest pain, palpitations, sick sinus syndrome

7 DRUG INTERACTIONS

7.1 Serotonergic Drugs

Serotonin syndrome (including altered mental status, autonomic instability, and neuromuscular symptoms) has been described following the concomitant use of 5-HT3 receptor antagonists and other serotonergic drugs, including selective serotonin reuptake inhibitors (SSRIs) and serotonin and noradrenaline reuptake inhibitors (SNRIs). Monitor for the emergence of serotonin syndrome. If symptoms occur, discontinue SANCUSO and initiate supportive treatment [see Warnings and Precautions (5.4)].

7.2 Concomitant Use Medications

There have been no definitive drug-drug interaction studies to examine pharmacokinetic or pharmacodynamic interaction with other drugs. However, in humans, granisetron hydrochloride injection has been safely administered with drugs representing benzodiazepines, neuroleptics and anti-ulcer medications commonly prescribed with antiemetic treatments. Granisetron hydrochloride injection also does not appear to interact with emetogenic cancer therapies. In agreement with these data, no clinically relevant drug interactions have been reported in clinical studies with SANCUSO.

8 USE IN SPECIFIC POPULATIONS

8.1 Pregnancy

Risk Summary

Available published data and postmarketing reports with granisetron use in pregnant women have not identified a drug-associated risk of major birth defects, miscarriage, or adverse maternal or fetal outcomes. In a published ex vivo human placental perfusion model, no transplacental passage of granisetron was detected at a concentration (5 ng/mL) that mimics the plasma concentration achieved following transdermal application of SANCUSO. In animal reproduction studies, no adverse developmental effects were observed in pregnant rats and rabbits administered granisetron hydrochloride during organogenesis at intravenous doses up to 24 times and 16 times, respectively, the maximum recommended human dose delivered by the SANCUSO transdermal system, based on body surface area (see Data).

The estimated background risk of major birth defects and miscarriage for the indicated population is unknown. All pregnancies have a background risk of birth defect, loss, or other adverse outcomes. In the U.S. general population, the estimated background risks of major birth defects and miscarriage in clinically recognized pregnancies are 2-4% and 15-20%, respectively.

In animal reproduction studies, no adverse developmental effects were observed in pregnant rats and rabbits administered granisetron hydrochloride at intravenous doses up to 24 times and 16 times, respectively, the maximum recommended human dose delivered by the SANCUSO transdermal system, based on body surface area (see Data).

Data

Animal Data

Reproduction studies with granisetron hydrochloride have been performed in pregnant rats at intravenous doses up to 9 mg/kg/day (54 mg/m^2/day, about 24 times the recommended human dose delivered by the SANCUSO transdermal system, based on body surface area) and oral doses up to 125 mg/kg/day (750 mg/m^2/day, about 326 times the recommended human dose with SANCUSO based on body surface area). Reproduction studies have been performed in pregnant rabbits at intravenous doses up to 3 mg/kg/day (36 mg/m^2/day, about 16 times the human dose with SANCUSO based on body surface area) and at oral doses up to 32 mg/kg/day (384 mg/m^2/day, about 167 times the human dose with SANCUSO based on body surface area). These studies did not reveal any harm to the fetus due to granisetron.

8.2 Lactation

Risk Summary

There are no data on the presence of granisetron in human milk, the effects on the breastfed child, or the effects on milk production. The developmental and health benefits of breastfeeding should be considered along with the mother's clinical need for SANCUSO and any potential adverse effects on the breastfed child from SANCUSO or from the underlying maternal condition.

8.4 Pediatric Use

Safety and effectiveness of SANCUSO have not been established in pediatric patients.

8.5 Geriatric Use

Clinical studies of SANCUSO did not include sufficient numbers of subjects aged 65 and over to determine whether they respond differently from younger subjects. Other reported clinical experience has not identified differences in responses between the elderly and younger patients. In general, cautious treatment selection for an elderly patient is prudent because of the greater frequency of decreased hepatic, renal, or cardiac function, and of concomitant disease or other drug therapy.

8.6 Renal Impairment or Hepatic Impairment

Although no studies have been performed to investigate the pharmacokinetics of SANCUSO in patients with renal or hepatic impairment, pharmacokinetic information is available for intravenous granisetron [see Clinical Pharmacology (12.3)]. No dosage adjustment is recommended for renal or hepatic impairment.

10 OVERDOSAGE

There is no specific antidote for granisetron overdosage. In the case of overdosage, symptomatic treatment should be given.

11 DESCRIPTION

SANCUSO contains granisetron, which is a serotonin-3 (5-HT3) receptor antagonist. Chemically it is 1-methyl-N-[(1R,3r,5S)-9-methyl-9-azabicyclo[3.3.1]non-3-yl]-1H-indazole-3-carboxamide with a molecular weight of 312.4. Its empirical formula is C18H24N4O, while its chemical structure is:

Granisetron is a white to off-white solid that is insoluble in water. The inactive ingredients are acrylate-vinylacetate copolymer, polyester, titanium dioxide, polyamide resin and polyethylene wax. SANCUSO is a 52 cm^2 thin, translucent, matrix-type transdermal system that is rectangular- shaped with rounded corners, consisting of a backing (polyester), the drug matrix (acrylate- vinylacetate copolymer) and a release liner (siliconized polyester).

12 CLINICAL PHARMACOLOGY

12.1 Mechanism of Action

Granisetron is a selective 5-hydroxytryptamine3 (5-HT3) receptor antagonist with little or no affinity for other serotonin receptors, including 5-HT1, 5-HT1A, 5-HT1B/C, 5-HT2; for alpha1-, alpha2-, or beta-adrenoreceptors; for dopamine-D2; or for histamine-H1; benzodiazepine; picrotoxin or opioid receptors.

Serotonin receptors of the 5-HT3 type are located peripherally on vagal nerve terminals and centrally in the chemoreceptor trigger zone of the area postrema. During chemotherapy that induces vomiting, mucosal enterochromaffin cells release serotonin, which stimulates 5-HT3 receptors. This evokes vagal afferent discharge, inducing vomiting. Animal studies demonstrate that, in binding to 5-HT3 receptors, granisetron blocks serotonin stimulation and subsequent vomiting after emetogenic stimuli such as cisplatin. In the ferret animal model, a single granisetron injection prevented vomiting due to high-dose cisplatin or arrested vomiting within 5 to 30 seconds.

12.2 Pharmacodynamics

The effect of granisetron on QTc prolongation was evaluated in a randomized, single-blind, positive (moxifloxacin 400 mg) - and placebo controlled parallel study in healthy subjects. A total of 120 subjects were administered SANCUSO transdermal system (n=60) or intravenous granisetron (10 mcg/kg over 30 seconds; n=60). In a study with demonstrated ability to detect small effects, the upper bound of the 90% confidence interval for the largest placebo adjusted, baseline corrected QTc based on Fridericia correction method (QTcF) for SANCUSO was below 10 ms. This study suggests that SANCUSO does not have significant effects on QT prolongation.

No evidence of an effect on plasma prolactin or aldosterone concentrations has been found in studies using granisetron.

The effect on oro-cecal transit time following application of SANCUSO has not been studied. Granisetron hydrochloride injection exhibited no effect on oro-cecal transit time in healthy subjects given a single intravenous infusion of 50 mcg/kg or 200 mcg/kg. Single and multiple oral doses of granisetron hydrochloride slowed colonic transit in healthy subjects.

12.3 Pharmacokinetics

Absorption

Granisetron crosses intact skin into the systemic circulation by a passive diffusion process.

Following a 7-day application of SANCUSO transdermal system in 24 healthy subjects, high inter- subject variability in systemic exposure was observed. Maximal concentration was reached at approximately 48 hours (range: 24-168 hours) following application. Mean Cmax was 5 ng/mL (CV: 170%) and mean AUC0-168hr was 527 ng-hr/mL (CV: 173%).

Mean Plasma Concentration of Granisetron (mean ± SD)

Based on the measure of residual content of the transdermal system after removal, approximately 66% (SD: ± 10.9) of granisetron is delivered following transdermal system application for 7 days.

Following consecutive application of two SANCUSO transdermal systems, each for seven days, granisetron plasma concentrations were maintained over the study period with evidence of minimal accumulation. The mean plasma concentration at 24 hours after the second transdermal system application was 1.5-fold higher due to residual granisetron from the first transdermal system. As the plasma concentration increased after the second transdermal system application, the difference decreased and the mean plasma concentration at 48 hours was 1.3-fold higher after application of the second transdermal system compared to that after application of the first transdermal system.

In a study designed to assess the effect of heat on the transdermal delivery of granisetron from SANCUSO in healthy subjects, a heat pad generating an average temperature of 42°C (107.6°F) was applied over the transdermal system for 4 hours each day over the 5 day period of wear. The application of the heat pad was associated with an increase in plasma granisetron concentrations during the period of heat pad application. The elevated plasma concentration declined after removal of the heat pad. Mean Cmax with intermittent heat exposure was 6% higher than without heat. Mean partial AUCs over 6 hours with 4 hour of heat application (AUC0-6, AUC24-30, and AUC48-54) were 4.9, 1.4, and 1.1 fold higher, respectively, with heat pad than without heat pad [see Dosage and Administration (2), Warnings and Precautions (5.4)].

Distribution

Plasma protein binding is approximately 65%. Granisetron distributes freely between plasma and red blood cells.

Elimination

Metabolism

Granisetron metabolism involves N-demethylation and aromatic ring oxidation followed by conjugation. In vitro liver microsomal studies show that granisetron's major route of metabolism is inhibited by ketoconazole, suggestive of metabolism mediated by the cytochrome P-450 3A subfamily. Animal studies suggest that some of the metabolites may also have 5-HT3 receptor antagonist activity.

Excretion

Clearance is predominantly by hepatic metabolism. Based on a study with intravenous injection, approximately 12% of the dose is excreted unchanged in the urine of healthy subjects in 48 hours. The remainder of the dose is excreted as metabolites, 49% in the urine, and 34% in the feces.

Use in Specific Populations

Geriatric Patients

Following application of SANCUSO transdermal system in healthy subjects, mean AUC0-z, Cmax, and Cavg were 17%, 15%, and 16% higher, respectively in male and female elderly subjects (≥ 65 years) compared to younger subjects (aged 18-45 years inclusive). These pharmacokinetic parameters were largely overlapped between the two age groups with high variability (CV: >50%).

Following a single 40 mcg/kg intravenous dose of granisetron hydrochloride in elderly subjects (mean age 71 years), lower clearance and longer half-life were observed compared to younger healthy subjects.

Male and Female Patients

There is evidence to suggest that female subjects had higher granisetron concentrations than males following transdermal system application. However, no statistically significant difference in clinical efficacy outcome was observed between males and females.

Racial or Ethnic Groups

The pharmacokinetic profile of granisetron from SANCUSO was assessed in healthy Japanese males. Following the application of a single 6-day SANCUSO 52 cm^2 transdermal system, in healthy male Japanese subjects, mean Cmax, AUC(0-144), and AUC(0-∞) values were 5.02 ng/mL (CV: 66%), 492 ng.hr/mL (CV: 72%), and 562 ng.hr/mL (CV: 60%), respectively, and a median tmax value was 48 hours.

Patients with Renal Impairment

Total clearance of granisetron was not affected in patients with severe renal failure who received a single 40 mcg/kg intravenous dose of granisetron hydrochloride.

Patients with Hepatic Impairment

In patients with hepatic impairment due to neoplastic liver involvement, total plasma clearance following a single 40 mcg/kg intravenous dose of granisetron hydrochloride was approximately halved compared to patients without hepatic impairment. Given the wide variability in pharmacokinetic parameters of granisetron and the good tolerance of doses well above the recommended dose, dose adjustment in patients with hepatic functional impairment is not necessary.

Body Mass Index

In a clinical study designed to assess granisetron exposure from SANCUSO in subjects with differing levels of body fat, using body mass index (BMI) as a surrogate measure for subcutaneous fat, no significant differences were seen in the plasma pharmacokinetics of SANCUSO in male and female subjects with low BMI [<19.5 kg/m^2 (males), <18.5 kg/m^2 (females)] and high BMI (30.0 to 39.9 kg/m^2 inclusive) compared to a control group (BMI 20.0 to 24.9 kg/m^2 inclusive).

Drug Interaction Studies

Because granisetron is metabolized by hepatic cytochrome P-450 drug-metabolizing enzymes (CYP1A1 and CYP3A4), inducers or inhibitors of these enzymes may change the clearance and hence, the half-life of granisetron. In addition, the activity of the cytochrome P-450 subfamily 3A4 (involved in the metabolism of some of the main narcotic analgesic agents) is not modified by granisetron hydrochloride in vitro. In in vitro human microsomal studies, ketoconazole inhibited ring oxidation of granisetron hydrochloride. However, the clinical significance of in vivo pharmacokinetic interactions with ketoconazole is not known. In a human pharmacokinetic study, hepatic enzyme induction with phenobarbital resulted in a 25% increase in total plasma clearance of intravenous granisetron hydrochloride. The clinical significance of this change is not known.

13 NONCLINICAL TOXICOLOGY

13.1 Carcinogenesis, Mutagenesis, Impairment of Fertility

In a 24-month carcinogenicity study, rats were treated orally with granisetron 1, 5 or 50 mg/kg/day (6, 30 or 300 mg/m^2/day). The 50 mg/kg/day dose was reduced to 25 mg/kg/day (150 mg/m^2/day) during week 59 due to toxicity. For a 50 kg person of average height (1.46 m^2 body surface area), these doses represent about 2.6, 13, and 65 times the recommended clinical dose (3.1 mg/day, 2.3 mg/m^2/day, delivered by the SANCUSO transdermal system, on a body surface area basis). There was a statistically significant increase in the incidence of hepatocellular carcinomas and adenomas in males treated with 5 mg/kg/day (30 mg/m^2/day, about 13 times the recommended human dose with SANCUSO, on a body surface area basis) and above, and in females treated with 25 mg/kg/day (150 mg/m^2/day, about 65 times the recommended human dose with SANCUSO, on a body surface area basis). No increase in liver tumors was observed at a dose of 1 mg/kg/day (6 mg/m^2/day, about 2.6 times the recommended human dose with SANCUSO, on a body surface area basis) in males and 5 mg/kg/day (30 mg/m^2/day, about 13 times the recommended human dose with SANCUSO, on a body surface area basis) in females.

In a 12-month oral toxicity study, treatment with granisetron 100 mg/kg/day (600 mg/m^2/day, about 261 times the recommended human dose with SANCUSO, on a body surface area basis) produced hepatocellular adenomas in male and female rats while no such tumors were found in the control rats. A 24-month mouse carcinogenicity study of granisetron did not show a statistically significant increase in tumor incidence, but the study was not conclusive.

Because of the tumor findings in rat studies, SANCUSO should be prescribed only at the dose and for the indication recommended [see Indications and Usage (1), Dosage and Administration (2)].

Granisetron was not mutagenic in an in vitro Ames test and mouse lymphoma cell forward mutation assay, and in vivo mouse micronucleus test and in vitro and ex vivo rat hepatocyte UDS assays. It, however, produced a significant increase in UDS in HeLa cells in vitro and a significant increased incidence of cells with polyploidy in an in vitro human lymphocyte chromosomal aberration test.

Granisetron at subcutaneous doses up to 6 mg/kg/day (36 mg/m^2/day, about 16 times the recommended human dose of SANCUSO, on a body surface area basis), and oral doses up to 100 mg/kg/day (600 mg/m^2/day, about 261 times the recommended human dose of SANCUSO, on a body surface area basis) was found to have no effect on fertility and reproductive performance of male and female rats.

13.3 Phototoxicity

When tested for potential photogenotoxicity in vitro in a Chinese hamster ovary (CHO) cell line, at 200 and 300 mcg/mL, granisetron increased the percentage of cells with chromosomal aberration following photoirradiation [see Warnings and Precautions (5.5)].

Granisetron was not phototoxic when tested in vitro in a mouse fibroblast cell line. When tested in vivo in guinea-pigs, SANCUSO transdermal system did not show any potential for photoirritation or photosensitivity. No phototoxicity studies have been performed in humans.

14 CLINICAL STUDIES

The effectiveness of SANCUSO in the prevention of chemotherapy-induced nausea and vomiting (CINV) was evaluated in a randomized, parallel group, double-blind, double-dummy study conducted in the U.S. and abroad. The study compared the efficacy, tolerability and safety of SANCUSO transdermal system with that of 2 mg oral granisetron once daily in the prevention of nausea and vomiting in a total of 641 patients receiving multi-day chemotherapy.

The population randomized into the trial included 48% males and 52% females aged 16 to 86 years receiving moderately emetogenic (ME) or highly emetogenic (HE) multi-day chemotherapy. Seventy-eight (78%) of patients were White, 12% Asian, 10% Hispanic/Latino and 0% Black.

SANCUSO was applied 24 to 48 hours before the first dose of chemotherapy and kept in place for 7 days. Oral granisetron was administered daily for the duration of the chemotherapy regimen, 1hour before each dose of chemotherapy. Efficacy was assessed from the first administration until 24 hours after the start of the last day's administration of the chemotherapy regimen.

The primary endpoint of the trial was the proportion of patients achieving no vomiting and/or retching, no more than mild nausea and no rescue medication from the first administration until 24 hours after the start of the last day's administration of multi-day chemotherapy. Using this definition, the effect of SANCUSO was established in 60.2% of patients in the SANCUSO arm and 64.8% of patients receiving oral granisetron (difference -4.89%; 95% confidence interval – 12.91% to +3.13%).

An assessment of transdermal system adhesion in 621 patients receiving either active or placebo transdermal system showed that less than 1% of transdermal systems became detached over the course of the 7 day period of transdermal system application.

16 HOW SUPPLIED/STORAGE AND HANDLING

SANCUSO (granisetron transdermal system) is a 52 cm^2 thin, translucent, rectangular-shaped transdermal system with rounded corners imprinted on one side with "Granisetron 3.1 mg/24 hours". The transdermal system releases 3.1 mg of granisetron per 24 hours for up to 7 days.

Each SANCUSO transdermal system is packaged in a separate sealed foil-lined plastic pouch supplied in packages of 1 (NDC 66220-637-31) transdermal system.

Store at 20°-25°C (68°-77°F); excursions permitted between 15°-30°C (59°-86°F). [see USP Controlled Room Temperature].

SANCUSO should be stored in the original packaging.

17 PATIENT COUNSELING INFORMATION

Advise the patient to read the FDA-approved patient labeling (Patient Information).

Progressive Ileus and Gastric Distention

Advise the patient to report new or worsening constipation to their healthcare provider and seek immediate medical care if symptoms of an ileus (pain or swelling in their abdomen) occur [see Warnings and Precautions (5.1)].

Serotonin Syndrome

Advise the patient of the possibility of serotonin syndrome with concomitant use of SANCUSO and another serotonergic agent such as medications to treat depression and migraines. Advise the patient to seek immediate medical attention if the following symptoms occur: changes in mental status, autonomic instability, neuromuscular symptoms, with or without gastrointestinal symptoms [see Warnings and Precautions (5.2)].

Skin Reactions

Instruct the patient remove the transdermal system if they have a severe skin reaction, or a generalized skin reaction (e.g. allergic rash, including erythematous, macular, papular rash or pruritus) [see Warnings and Precautions (5.3)].

Increased Drug Exposure with Use of External Heat Sources

Advise the patient to avoid prolonged exposure to heat and not to apply a heat pad or heat lamp over or near the SANCUSO transdermal system and avoid extended exposure to heat [see Warnings and Precautions (5.4)].

Phototoxicity with Ultraviolet Light Exposure

Advise the patient to avoid direct sunlight or exposure to sunlamps and to cover the application site of the transdermal system with clothing, if there is a risk of exposure to sunlight or sunlamps throughout the period of wear and for 10 days following its removal [see Warnings and Precautions (5.5)].

Application and Removal Instructions

Instruct the patient on how to apply and remove the transdermal system:

- Only wear one transdermal system at any time.
- Do not cut the transdermal system.
- Apply the transdermal system to clean, dry, nearly hairless, intact healthy skin on the upper outer arm.
- After the transdermal system is applied, wash hands thoroughly.
- Remove the transdermal system by peeling off gently from the skin.
- Upon removal, fold the used transdermal system in half with the sticky side together, and discard in household trash in a manner that prevents accidental contact or ingestion by children, pets or others.
- SANCUSO contains granisetron. Do not use other granisetron-containing products with SANCUSO [see Dosage and Administration (2)].

Manufactured by:
Kindeva Drug Delivery L.P.
Northridge, CA 91324

Manufactured for:
Cumberland Pharmaceuticals Inc.
Nashville, TN 37203

US Patent Number 7608282
SANCUSO® is a registered trademark of Cumberland Pharmaceuticals Inc.

Patient Information
SANCUSO® [san-KOO-so]
(granisetron transdermal system)
for transdermal use

Important: For skin use only.

Read the Patient Information that comes with SANCUSO before you start using it and each time you get a refill. There may be new information. This information does not take the place of talking to your healthcare provider about your medical condition or your treatment. If you have any questions about SANCUSO, ask your healthcare provider.

What is SANCUSO?
SANCUSO is a prescription medicine used to prevent nausea and vomiting in adults receiving anti-cancer (chemotherapy) treatment that causes moderate or severe vomiting.
SANCUSO is a skin patch (transdermal system) that slowly releases the medicine into your bloodstream while you wear the transdermal system.
It is not known if SANCUSO is safe and effective in children.

Who should not use SANCUSO?
Do not use SANCUSO if you are allergic to granisetron or any of the ingredients in SANCUSO. See the end of this leaflet for a list of ingredients in SANCUSO.

What should I tell my healthcare provider before using SANCUSO? Before using SANCUSO, tell your healthcare provider about all of your medical conditions, including if you:

- have pain or swelling in your stomach area (abdomen).
- are pregnant. It is not known if SANCUSO will harm your unborn baby. Talk to your healthcare provider if you are pregnant or plan to become pregnant.
- are breastfeeding or plan to breastfeed. It is not known if SANCUSO passes into your breast milk.

Tell your healthcare provider about all the medicines you take, including prescription and over-the-counter medicines, vitamins and herbal supplements. Other medicines may affect how SANCUSO works. SANCUSO may also affect how other medicines work. SANCUSO contains granisetron. Do not take other granisetron containing products with SANCUSO.
Know the medicines you take. Keep a list of them to show your healthcare provider and pharmacist when you get a new medicine.

How should I use SANCUSO?

- Read the Instructions for Use that comes with SANCUSO transdermal system.
- Use SANCUSO exactly as your healthcare provider tells you to.

What should I avoid while using SANCUSO?
Do not apply any heat source over or near the SANCUSO transdermal system.

- A heating pad or heat lamp should not be used where the transdermal system is applied.
- You should avoid long periods of exposure to heat because heat can increase the amount of SANCUSO in your blood.
- Avoid sunlight and artificial sunlight. The medicine in SANCUSO may not work as well and may affect your skin if exposed to direct sunlight or artificial sunlight from sunlamps or tanning beds.
- Keep the transdermal system covered with clothing if you will be in direct sunlight or artificial sunlight.
- Keep the skin where SANCUSO was applied covered for another 10 days after the transdermal system is taken off to protect from exposure to direct sunlight or artificial sunlight.

What are the possible side effects of SANCUSO?
SANCUSO may cause serious side effects, including:

- Using SANCUSO may make it harder to identify certain stomach (abdomen) and bowel problems that are from other causes. Tell your healthcare provider if you have any abdominal pain or swelling while using SANCUSO.

- Serotonin Syndrome. A potentially life-threatening problem called serotonin syndrome can happen if you use SANCUSO with certain medicines. Call your healthcare provider or go to the nearest hospital emergency room right away if you have any of the following signs and symptoms of serotonin syndrome:
  - agitation
  - seeing or hearing things that are not real (hallucinations)
  - confusion
  - coma
  - fast heart beat
  - changes in blood pressure
  - dizziness
  - sweating
  - flushing
  - high body temperature (hyperthermia)
  - shaking (tremors), stiff muscles, or muscle twitching
  - loss of coordination
  - seizures
  - nausea, vomiting, diarrhea
- Skin reactions. Skin reactions can happen at the transdermal system application site or outside the transdermal system application site. Tell your healthcare provider if you get any redness, rashes, bumps, blisters or itching at or near the transdermal system application site, and especially if they spread outside the place where the transdermal system was applied or if they appear outside the transdermal system application site. You may need to stop using SANCUSO.

The most common side effects of SANCUSO include:

- constipation

Tell your healthcare provider if you have any side effect that bothers you or that does not go away. These are not all the possible side effects of SANCUSO. For more information, ask your healthcare provider or pharmacist.
Call your doctor for medical advice about side effects. You may report side effects to FDA at 1-800-FDA-1088.

How should I store SANCUSO?

- Store SANCUSO at room temperature between 68°F to 77°F (20°C to 25°C).
- Keep SANCUSO in the original package it comes in.

Keep SANCUSO out of the reach of children.

General information about the safe and effective use of SANCUSO.
Medicines are sometimes prescribed for purposes other than those listed in a Patient Information leaflet. Do not use SANCUSO for a condition for which it was not prescribed. Do not give SANCUSO to other people, even if they have the same symptoms that you have. It may harm them. This Patient Information leaflet summarizes the most important information about SANCUSO. You can ask your pharmacist or healthcare provider for information about SANCUSO that is written for health professionals.

Manufactured by:
Kindeva Drug Delivery L.P.
Northridge, CA 91324
Manufactured for:
Cumberland Pharmaceuticals Inc.
Nashville, TN 37203
For more information, go to www.sancuso.com or call 1-877-683-6110.

This Patient Information has been approved by the U.S. Food and Drug Administration

Revised: 07/2024

Instructions for Use SANCUSO® [san-KOO-so] (granisetron transdermal system) for transdermal use

Read this Instructions for Use before you start using SANCUSO transdermal system and each time you get a refill. There may be new information. This information does not take the place of talking to your healthcare provider about your medical condition or treatment.

Important Information:

- SANCUSO is for skin use only (transdermal system).
- Avoid exposing the SANCUSO transdermal system application site to direct heat sources such as a heating pad or heat lamp.
- Avoid exposing the SANCUSO transdermal system to direct sunlight or artificial light such as a sunlamp or tanning bed.
- Keep the SANCUSO transdermal system covered with clothing if you will be in sunlight or artificial sunlight.
- Keep the skin where the SANCUSO transdermal system was applied covered for another 10 days after the SANCUSO transdermal system is taken off, to protect from exposure to direct sunlight or artificial sunlight.
- Skin reactions can happen at the SANCUSO transdermal system application site or outside the SANCUSO transdermal system application site. Tell your healthcare provider if you get any redness, rashes, bumps, blisters or itching at the SANCUSO transdermal system application site, and especially if they spread outside the place where the SANCUSO transdermal system was applied or if they appear outside the SANCUSO transdermal system application site. You may need to stop using the SANCUSO transdermal system.

How should I store the SANCUSO transdermal system?

- Store the SANCUSO transdermal system at room temperature between 68°F to 77°F (20°C to 25°C).
- Keep the SANCUSO transdermal system in the original package it comes in.
- Do not open the package until you are ready to apply the SANCUSO transdermal system.

Supplies:

- SANCUSO transdermal system
- surgical or medical adhesive tape (not included)

When do I apply the SANCUSO transdermal system?

- Use the SANCUSO transdermal system exactly as your healthcare provider tells you to.
- Apply the SANCUSO transdermal system at least 1 day (24 hours) or up to 2 days (48 hours) before your scheduled anti-cancer (chemotherapy) treatment.
- Wear the SANCUSO transdermal system all the time during your chemotherapy treatment.
- Wait at least 1 day (24 hours) after your chemotherapy treatment is finished to remove the SANCUSO transdermal system.
- The SANCUSO transdermal system may be worn for up to 7 days.

Where do I apply the SANCUSO transdermal system?

- SANCUSO transdermal system should only be applied to the outside of the upper arm.
- Apply the SANCUSO transdermal system to a clean, dry, nearly hairless, healthy area of skin on the outside part of your upper arm. If there is hair, do not shave. Instead, clip hair as close to the skin as possible.
- The area you choose should not be oily or recently shaved. The SANCUSO transdermal system should not be placed on skin that is red, irritated, or damaged (cut or scraped).
- Do not apply the SANCUSO transdermal system to areas that have been treated with creams, oils, lotions, powders or other skin products that could keep the SANCUSO transdermal system from sticking well to your skin.

How do I apply the SANCUSO transdermal system?

The SANCUSO transdermal system comes inside a pouch which is inside the carton.

1. Do not remove the SANCUSO transdermal system from the pouch until you are ready to use it.
2. Do not cut the SANCUSO transdermal system into pieces.
3. Remove the pouch from the carton.
4. Tear the pouch open at the notch provided, and remove the SANCUSO transdermal system. Each pouch contains one SANCUSO transdermal system stuck onto a stiff (rigid) plastic film.
5. The unprinted, sticky side of the SANCUSO transdermal system is covered by a 2-piece stiff (rigid) plastic film. Bend the transdermal system in the middle. Slowly peel 1-half of the stiff (rigid) plastic film. Be careful not to stick the SANCUSO transdermal system to itself. Do not touch the sticky side of the SANCUSO transdermal system.
6. While holding the other half of the stiff (rigid) plastic film, apply the sticky half of the SANCUSO transdermal system to your skin. Remove the second half of the stiff (rigid) plastic film and press the whole SANCUSO transdermal system firmly in place and smooth it down with your fingers. Press firmly making sure the SANCUSO transdermal system sticks well to the skin, especially around the edges.
7. Wash your hands with soap and water right away after applying the SANCUSO transdermal system to remove any medicine that may have stuck to your fingers.
8. Keep the SANCUSO transdermal system in place for the whole time you are receiving your chemotherapy treatment. Remove the SANCUSO transdermal system at least 1 day (24 hours) after your chemotherapy treatment is finished. The SANCUSO transdermal system can be worn for up to 7 days, depending on the number of days your chemotherapy treatment lasts.
9. Do not re-use the SANCUSO transdermal system after you remove it. See the instructions below on the right way to remove and throw away the SANCUSO transdermal system.

What do I do if the SANCUSO transdermal system does not stick well?

If the SANCUSO transdermal system does not stick well or the edges lift off the skin, you may apply pieces of surgical or medical adhesive tape on each lifted edge to keep the SANCUSO transdermal system in place. Only place pieces of the surgical or medical adhesive tape on the edges of the SANCUSO transdermal system. Do not completely cover the SANCUSO transdermal system with surgical or medical adhesive tape and do not wrap completely around your arm. If the SANCUSO transdermal system comes more than half off or it becomes damaged (e.g. rips), contact your healthcare provider.

Can I bathe or shower while wearing the SANCUSO transdermal system?

You can continue to shower and wash normally while wearing the SANCUSO transdermal system.

It is not known how other activities, for example swimming, strenuous exercise or using a sauna or whirlpool, may affect the SANCUSO transdermal system. Avoid these activities while wearing the SANCUSO transdermal system.

How do I remove and dispose of the SANCUSO transdermal system?

1. When you remove the SANCUSO transdermal system, peel it off gently.
2. The used SANCUSO transdermal system will still contain some of the medicine. After removing the used SANCUSO transdermal system, fold it in half so that the sticky side sticks to itself. Throw away the used SANCUSO transdermal system in the trash right away so that children and pets cannot reach it.
3. If any adhesive (glue) remains on your skin after you remove the SANCUSO transdermal system, wash the area with soap and water to remove it. Do not use alcohol or other dissolving liquids, such as nail polish remover. These may cause skin irritation.
4. Wash your hands with soap and water after handling the SANCUSO transdermal system.
5. You may see mild redness on the skin where the SANCUSO transdermal system is removed. This redness should go away within 3 days. If redness continues, tell your healthcare provider.

What are the ingredients in the SANCUSO transdermal system?

Active ingredient: granisetron.

Inactive ingredients: acrylate-vinylacetate copolymer, polyester, titanium dioxide, polyamide resin and polyethylene wax. This Instructions for Use has been approved by the U.S. Food and Drug Administration.

Manufactured by:
Kindeva Drug Delivery L.P.
Northridge, CA 91324

Manufactured for:
Cumberland Pharmaceuticals Inc., Nashville, TN 37203

Revised: 07/2024

Principal Display Panel – 168 h Pouch Label

Sancuso®

(Granisetron Transdermal System)

3.1 mg/24 hours

NDC 66220-637-31

7 day transdermal system

Each 52 cm^2 transdermal system
contains 34.3 mg of granisetron.

For Transdermal Use Only.

Read patient information before use.
Do not cut the transdermal system.
Keep out of the reach of children.
Store at 20° to 25°C (68° to 77°F).
Keep pouch in outer carton.
Rx Only

Includes 1 transdermal system

Mfd. for:

Cumberland Pharmaceuticals Inc.

Nashville, TN 37203

CUMBERLAND®
PHARMACEUTICALS